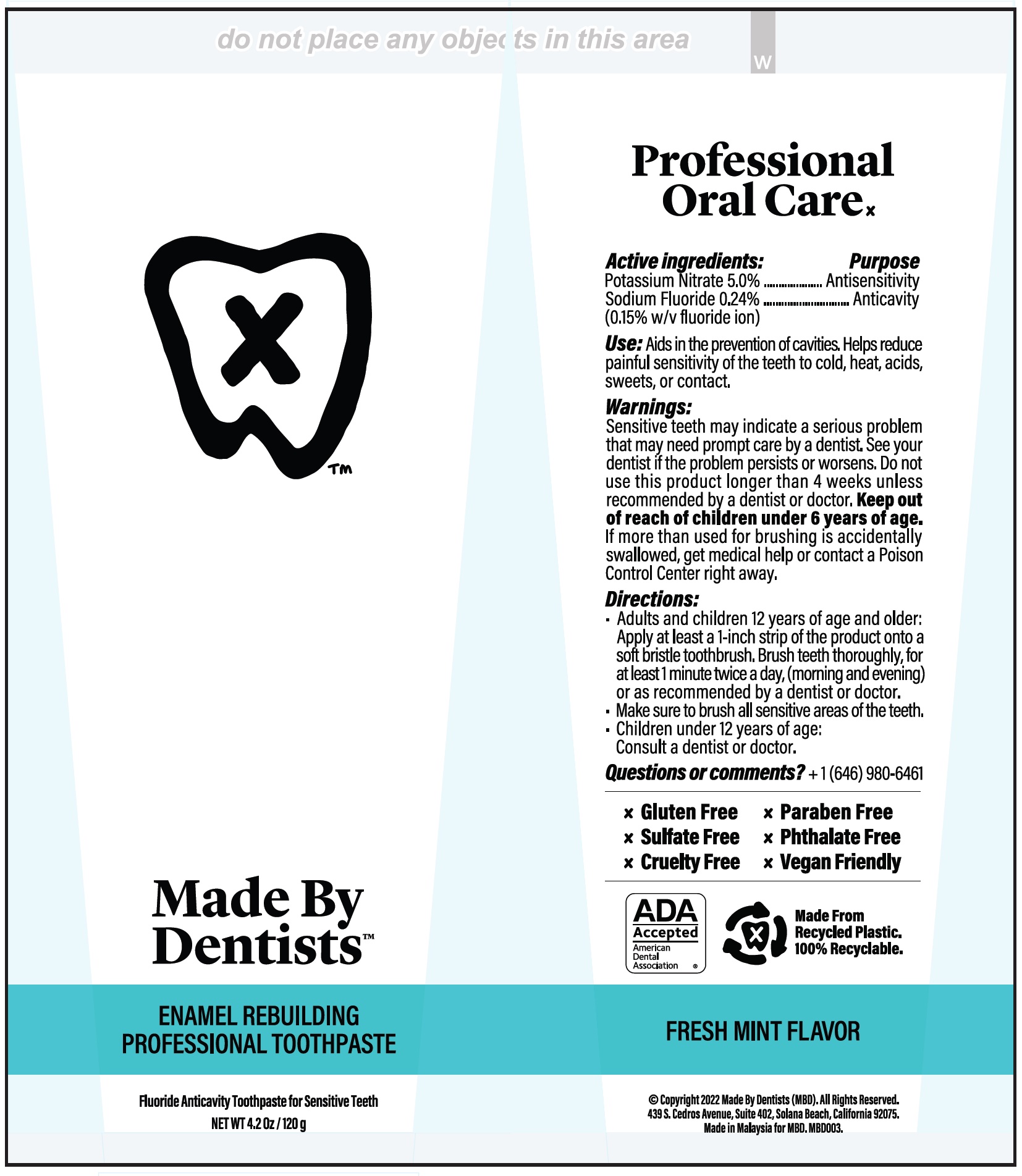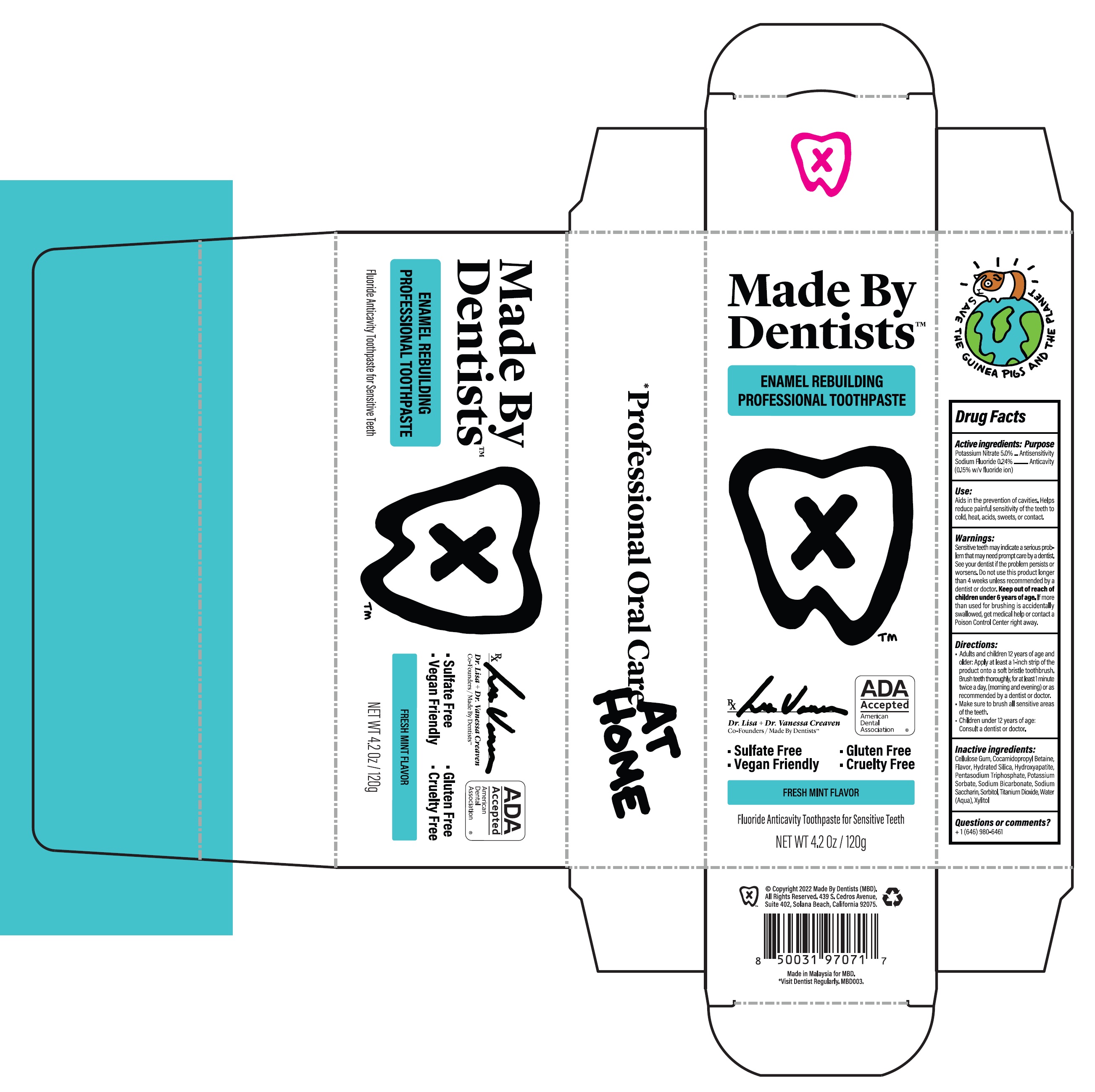 DRUG LABEL: Made by Dentists Enamel Rebuilding Professional
NDC: 62776-003 | Form: PASTE
Manufacturer: Fulijaya Manufacturing Sdn. Bhd
Category: otc | Type: HUMAN OTC DRUG LABEL
Date: 20250623

ACTIVE INGREDIENTS: POTASSIUM NITRATE 50 mg/1 g; SODIUM FLUORIDE 1.5 mg/1 g
INACTIVE INGREDIENTS: CARBOXYMETHYLCELLULOSE SODIUM, UNSPECIFIED; COCAMIDOPROPYL BETAINE; HYDRATED SILICA; TRIBASIC CALCIUM PHOSPHATE; SODIUM TRIPOLYPHOSPHATE ANHYDROUS; POTASSIUM SORBATE; SODIUM BICARBONATE; SACCHARIN SODIUM; SORBITOL; TITANIUM DIOXIDE; WATER; XYLITOL

Made by Dentists Enamel Rebuilding Professional

Active ingredient:

Potassium Nitrate 5.0%

Sodium Fluoride 0.24% (0.15% w/v fluoride ion)

Purpose

Antisensitivity

Anticavity

Use:

Aids in the prevention of cavities. Helps reduce painful sensitivity of the teeth to cold, heat, acids, sweets, or contact.

Warnings:

Sensitive teeth may indicate a serious problem that may need prompt care by a dentist. See your dentist if the problem persists or worsens. Do not use this product longer than 4 weeks unless recommended by a dentist or doctor.

Keep out of reach of children under 6 years of age.

If more than used for brushing is accidentlly swallowed, get medical help or contact a Poison Control Center right away.

Directions:

- Adults and children 12 years of age and older: Apply at least a 1-inch strip of the product onto a soft bristle toothbrush. Brush teeth thoroughly, for at least 1 minute twice a day, (morning and evening) or as recommended by a dentist or doctor.
- Make sure to brush all sensitive areas of the teeth.
- Children under 12 years of age: Consult a dentist or doctor.

Inactive ingredients:

Cellulose Gum, Cocamidopropyl Betaine, Flavor, Hydrated Silica, Hydroxyapatite, Pentasodium Triphosphate, Potassium Sorbate, Sodium Bicarbonate, Sodium Saccharin, Sorbitol, Titanium Dioxide, Water (Aqua), Xylitol

Questions or comments?

+ 1 (646) 980-6461